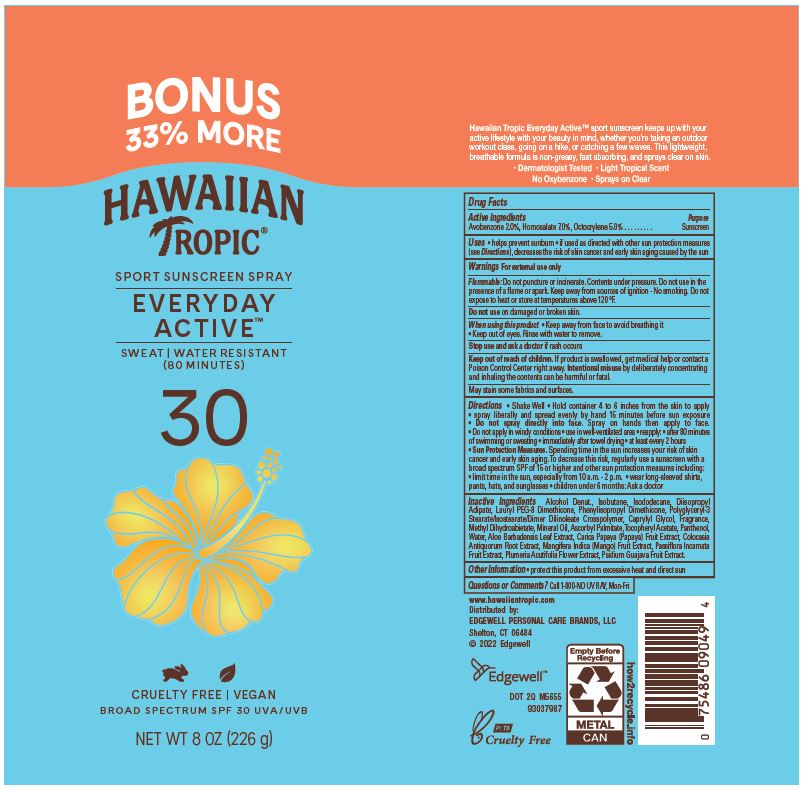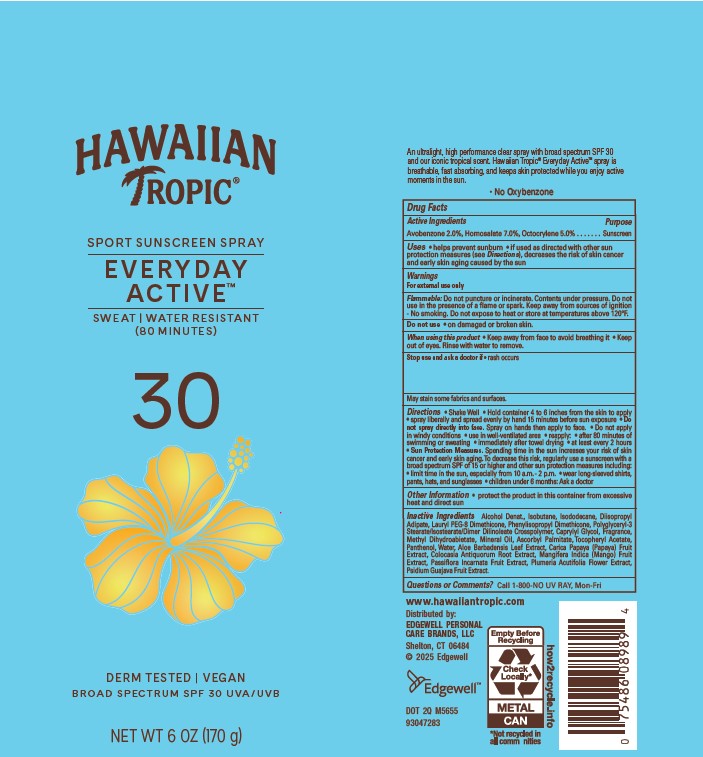 DRUG LABEL: HAWAIIAN TROPIC
NDC: 63354-299 | Form: AEROSOL, SPRAY
Manufacturer: Edgewell Personal Care Brands LLC
Category: otc | Type: HUMAN OTC DRUG LABEL
Date: 20251231

ACTIVE INGREDIENTS: HOMOSALATE 7 g/100 g; OCTOCRYLENE 5 g/100 g; AVOBENZONE 2 g/100 g
INACTIVE INGREDIENTS: METHYL DIHYDROABIETATE; ALPHA-TOCOPHEROL ACETATE; PANTHENOL; MINERAL OIL; MANGO; GUAVA; LAURYL PEG-8 DIMETHICONE (300 CPS); CAPRYLYL GLYCOL; DIISOPROPYL ADIPATE; PAPAYA; ALCOHOL; COLOCASIA ESCULENTA ROOT; ALOE VERA LEAF; ISODODECANE; ASCORBYL PALMITATE; WATER; PASSIFLORA INCARNATA FRUIT; PLUMERIA RUBRA FLOWER; ISOBUTANE

Active Ingredients

Avobenzone 2.0%, Homosalate 7.0%, Octocrylene 5.0%

Purpose

Sunscreen

Uses

• helps prevent sunburn • if used as directed with other sun protection measures (see Directions), decreases the risk of skin cancer and early skin aging caused by the sun

Warnings

For external use only

Flammable: Do not puncture or incinerate. Contents under pressure. Do not use in the presence of a flame or spark. Keep away from sources of ignition - No smoking. Do not expose to heat or store at temperatures above 120°F.

May stain some fabrics and surfaces.

Do not use

on damaged or broken skin.

When using this product

• Keep away from face to avoid breathing it • Keep out of eyes. Rinse with water to remove.

Stop use and ask a doctor

if rash occurs

Keep out of reach of children.

If product is swallowed, get medical help or contact a Poison Control Center right away. Intentional misuse by deliberately concentrating and inhaling the contents can be harmful or fatal.

Directions

• Shake Well • Hold container 4 to 6 inches from the skin to apply • spray liberally and spread evenly by hand 15 minutes before sun exposure • Do not spray directly into face. Spray on hands then apply to face. • Do not apply in windy conditions • use in well-ventilated area • reapply: • after 80 minutes of swimming or sweating • immediately after towel drying • at least every 2 hours • Sun Protection Measures. Spending time in the sun increases your risk of skin cancer and early skin aging. To decrease this risk, regularly use a sunscreen with a broad spectrum SPF of 15 or higher and other sun protection measures including: • limit time in the sun, especially from 10 a.m. - 2 p.m. • wear long-sleeved shirts, pants, hats, and sunglasses • children under 6 months: Ask a doctor

Inactive Ingredients

Alcohol Denat., Isobutane, Isododecane, Diisopropyl Adipate, Lauryl PEG-8 Dimethicone, Phenylisopropyl Dimethicone, Polyglyceryl-3 Stearate/Isostearate/Dimer Dilinoleate Crosspolymer, Caprylyl Glycol, Fragrance, Methyl Dihydroabietate, Mineral Oil, Ascorbyl Palmitate, Tocopheryl Acetate, Panthenol, Water, Aloe Barbadensis Leaf Extract, Carica Papaya (Papaya) Fruit Extract, Colocasia Antiquorum Root Extract, Mangifera Indica (Mango) Fruit Extract, Passiflora Incarnata Fruit Extract, Plumeria Acutifolia Flower Extract, Psidium Guajava Fruit Extract.

Other Information

• protect this product from excessive heat and direct sun

Questions or Comments?

Call 1-800-NO UV RAY, Mon-Fri

Principal Display Panel

HAWAIIAN
TROPIC(R)
SPORT SUNSCREEN SPRAY
EVERYDAY
ACTIVE(TM)
SWEAT | WATER RESISTANT
(80 MINUTES)
30
DERM TESTED | VEGAN
BROAD SPECTRUM SPF 30 UVA/UVB

NET WT 6 OZ (170 g)

BONUS

33% MORE

HAWAIIAN
TROPIC(R)
SPORT SUNSCREEN SPRAY
EVERYDAY
ACTIVE(TM)
SWEAT | WATER RESISTANT
(80 MINUTES)
30
CRUELTY FREE | VEGAN
BROAD SPECTRUM SPF 30 UVA/UVB
NET WT 8 OZ (226 g)